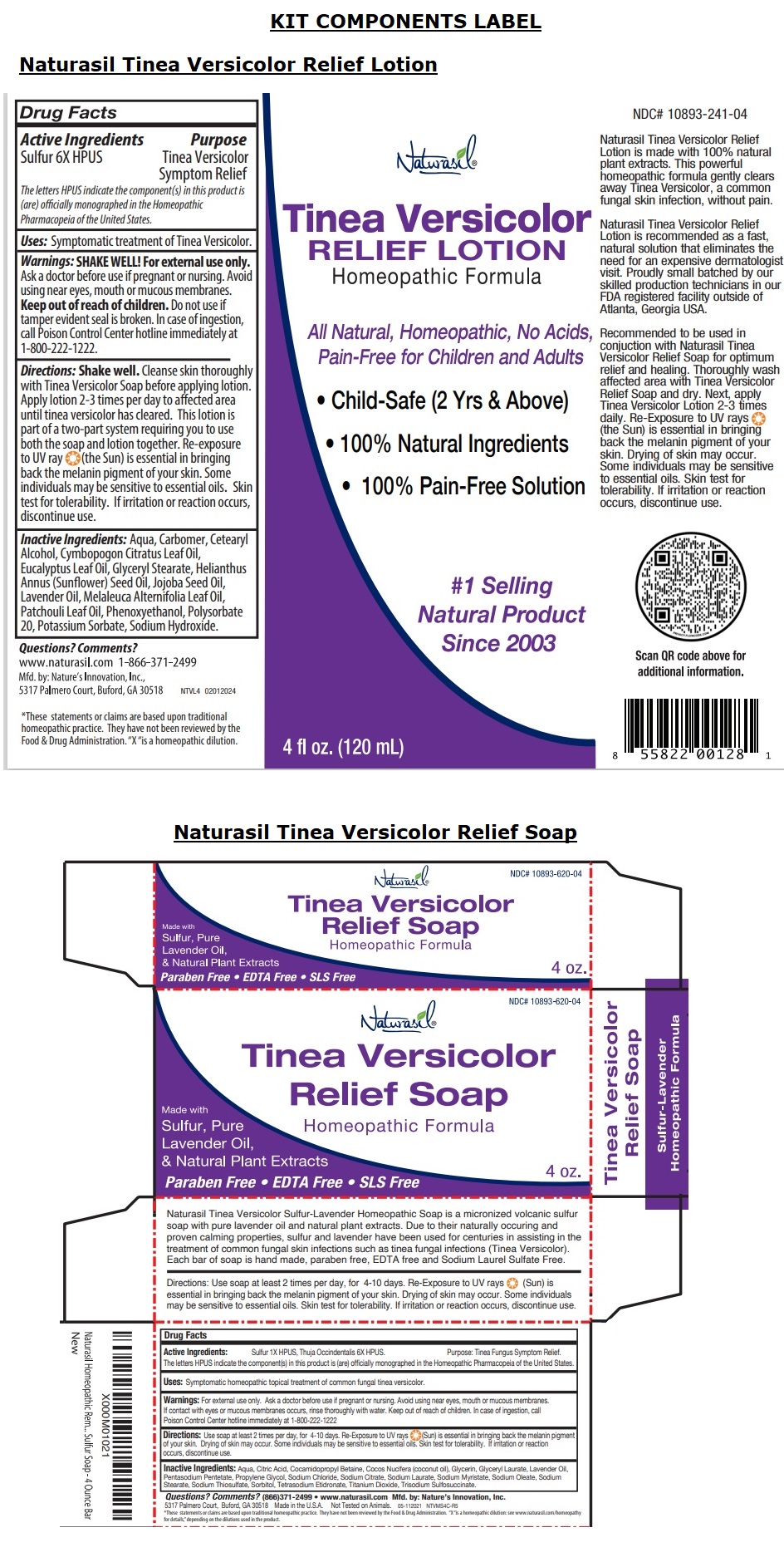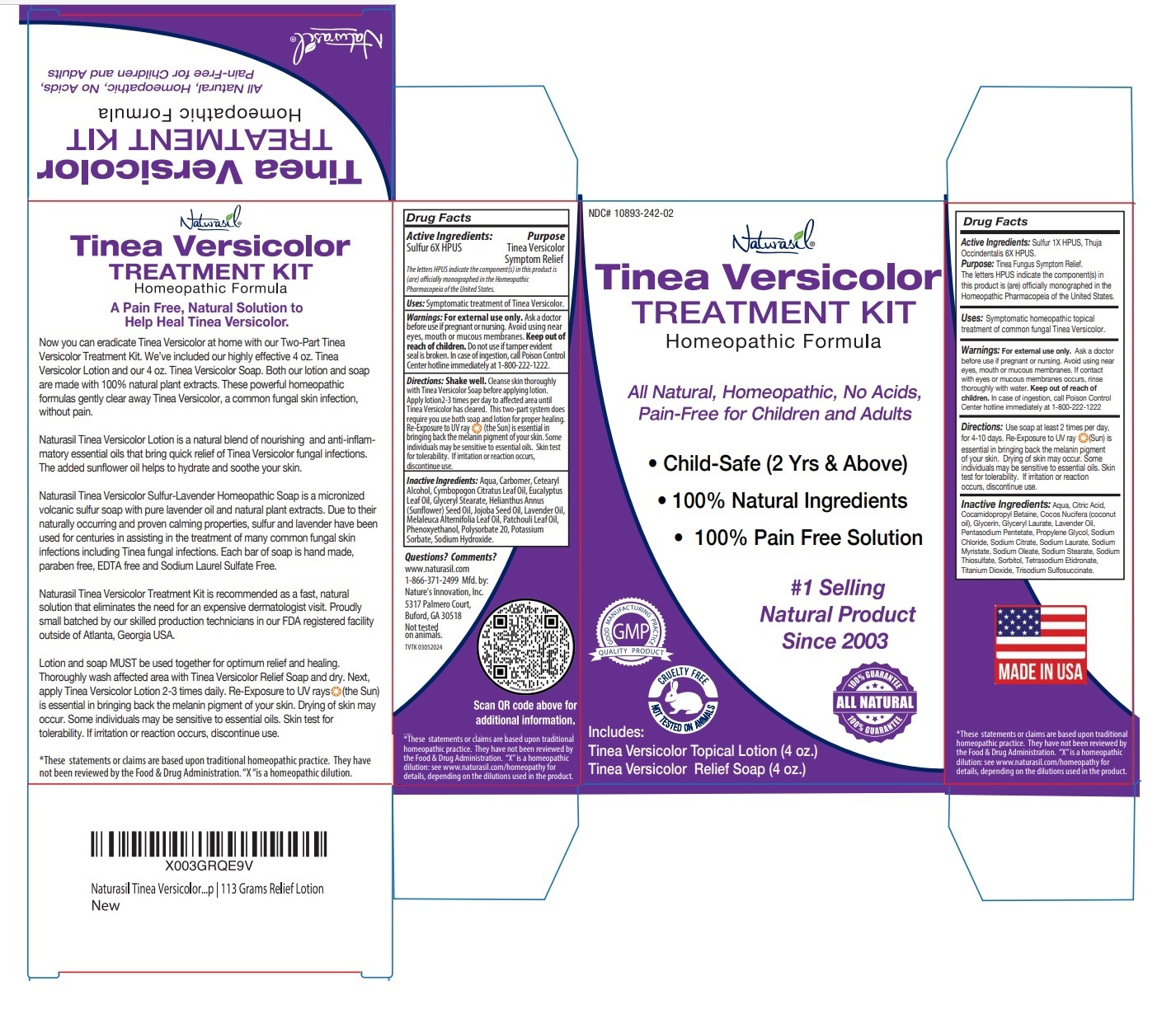 DRUG LABEL: Naturasil Tinea Versicolor Treatment kit
NDC: 10893-242 | Form: KIT | Route: TOPICAL
Manufacturer: Nature's Innovation, Inc.
Category: homeopathic | Type: HUMAN OTC DRUG LABEL
Date: 20240314

ACTIVE INGREDIENTS: SULFUR 6 [hp_X]/120 mL; SULFUR 1 [hp_X]/1 g; THUJA OCCIDENTALIS LEAFY TWIG 6 [hp_X]/1 g
INACTIVE INGREDIENTS: WATER; CARBOMER HOMOPOLYMER, UNSPECIFIED TYPE; CETOSTEARYL ALCOHOL; WEST INDIAN LEMONGRASS OIL; EUCALYPTUS OIL; GLYCERYL MONOSTEARATE; SUNFLOWER OIL; JOJOBA OIL; LAVENDER OIL; TEA TREE OIL; POGOSTEMON HEYNEANUS LEAF OIL; PHENOXYETHANOL; POLYSORBATE 20; POTASSIUM SORBATE; SODIUM HYDROXIDE; WATER; CITRIC ACID MONOHYDRATE; COCAMIDOPROPYL BETAINE; COCONUT OIL; GLYCERIN; GLYCERYL LAURATE; LAVENDER OIL; PENTASODIUM PENTETATE; PROPYLENE GLYCOL; SODIUM CHLORIDE; SODIUM CITRATE, UNSPECIFIED FORM; SODIUM LAURATE; SODIUM MYRISTATE; SODIUM OLEATE; SODIUM STEARATE; SODIUM THIOSULFATE; SORBITOL; ETIDRONATE TETRASODIUM; TITANIUM DIOXIDE; TRISODIUM SULFOSUCCINATE

Naturasil Tinea Versicolor Treatment kit

Naturasil Tinea Versicolor Relief Lotion

Drug Facts

Active Ingredients:

Sulfur 6X HPUS

The letters HPUS indicate the component(s) in this product is (are) officially monographed in the Homeopathic Pharmacopeia of the United States.

Purpose

Tinea Versicolor Symptom Relief

Uses:

Symptomatic treatment of Tinea Versicolor.

Warnings:

For external use only.
Ask a doctor before use if pregnant or nursing. Avoid using near eyes, mouth or mucous membranes.

Keep out of reach of children. Do not use if tamper evident seal is broken. In case of ingestion, call Poison Control Center hotline immediately at 1-800-222-1222.

Directions:

Shake well. Cleanse skin thoroughly with Tinea Versicolor Soap before applying lotion. Apply lotion 2-3 times per day to affected area until Tinea Versicolor has cleared. This two-part system does require you use both soap and lotion for proper healing. Re-Exposure to UV ray (the Sun) is essential in bringing back the melanin pigment of your skin. Some individuals may be sensitive to essential oils. Skin test for tolerability. If irritation or reaction occurs, discontinue use.

Inactive Ingredients:

Aqua, Carbomer, Cetearyl Alcohol, Cymbopogon Citratus Leaf Oil, Eucalyptus Leaf Oil, Glyceryl Stearate, Helianthus Annus (Sunflower) Seed Oil, Jojoba Seed Oil, Lavender Oil, Melaleuca Alternifolia Leaf Oil, Patchouli Leaf Oil, Phenoxyethanol, Polysorbate 20, Potassium Sorbate, Sodium Hydroxide.

Naturasil Tinea Versicolor Relief Soap

Drug Facts

Active Ingredients:

Sulfur 1X HPUS
Thuja Occidentalis 6X HPUS

The letters HPUS indicate the component(s) in this product is (are) officially monographed in the Homeopathic Pharmacopeia of the United States.

Purpose

Tinea Fungus Symptom Relief.

Uses:

Symptomatic homeopathic topical treatment of common fungal Tinea Versicolor.

Warnings:

For external use only.

Ask a doctor before use if pregnant or nursing. Avoid using near eyes, mouth or mucous membranes. If contact with eyes or mucous membranes occurs, rinse thoroughly with water.

Keep out of reach of children.

In case of ingestion, call Poison Control Center hotline immediately at 1-800-222-1222

Directions:

Use soap at least 2 times per day, for 4-10 days. Re-Exposure to UV ray (Sun) is essential in bringing back the melanin pigment of your skin. Drying of skin may occur. Some individuals may be sensitive to essential oils. Skin test for tolerability. If irritation or reaction occurs, discontinue use.

Inactive Ingredients:

Aqua, Citric Acid, Cocamidopropyl Betaine, Cocos Nucifera (coconut oil), Glycerin, Glyceryl Laurate, Lavender Oil, Pentasodium Pentetate, Propylene Glycol, Sodium Chloride, Sodium Citrate, Sodium Laurate, Sodium Myristate, Sodium Oleate, Sodium Stearate, Sodium Thiosulfate, Sorbitol, Tetrasodium Etidronate, Titanium Dioxide, Trisodium Sulfosuccinate.

Homeopathic Formula

All Natural, Homeopathic, No Acids, Pain-Free for Children and Adults

• Child-Safe (2 Yrs & Above)
• 100% Natural Ingredients
• 100% Pain-Free Solution

#1 Selling Natural product Since 2003

Now you can eradicate Tinea Versicolor at home with our Two-Part Tinea Versicolor Treatment Kit. We’ve included our highly effective 4 oz. Tinea Versicolor Lotion and our 4 oz. Tinea Versicolor Soap. Both our lotion and soap are made with 100% natural plant extracts. These powerful homeopathic formulas gently clear away Tinea Versicolor, a common fungal skin infection, without pain.

Naturasil Tinea Versicolor Lotion is a natural blend of nourishing and anti-inflammatory essential oils that bring quick relief of Tinea Versicolor fungal infections. The added Sunflower oil helps to hydrate and soothe your skin.

Naturasil Tinea Versicolor Sulfur-Lavender Homeopathic Soap is a micronized volcanic sulfur soap with pure lavender oil and natural plant extracts. Due to their naturally occurring and proven calming properties sulfur and lavender have been used for centuries in assisting in the treatment of many common fungal skin infections including Tinea fungal infections. Each bar of soap is hand made, paraben free, EDTA free and Sodium Laurel Sulfate Free.

Naturasil Tinea Versicolor Treatment Kit is recommended as a fast, natural solution that eliminates the need for an expensive dermatologist visit. Proudly small batched by our skilled production technicians in our FDA registered facility outside of Atlanta, Georgia USA.

Lotion and soap MUST be used together for optimum relief and healing. Thoroughly wash affected area with Tinea Versicolor Relief Soap and dry. Next, apply Tinea Versicolor Lotion 2-3 times daily. Re-Exposure to UV rays (the Sun) is essential in bringing back the melanin pigment of your skin. Drying of skin may occur. Some individuals may be sensitive to essential oils. Skin test for tolerability. If irritation or reaction occurs, discontinue use.

Questions? Comments?

www.naturasil.com

1-866-371-2499

Mfd. by: Nature’s Innovation, Inc.,
5317 Palmero Court, Buford, GA 30518

Not tested on animals.

MADE IN USA

*These statements or claims are based upon traditional homeopathic practice. They have not been reviewed by the Food & Drug Administration. “X” is a homeopathic dilution: see www.naturasil.com/homeopathy for details, depending on the dilutions used in the product.